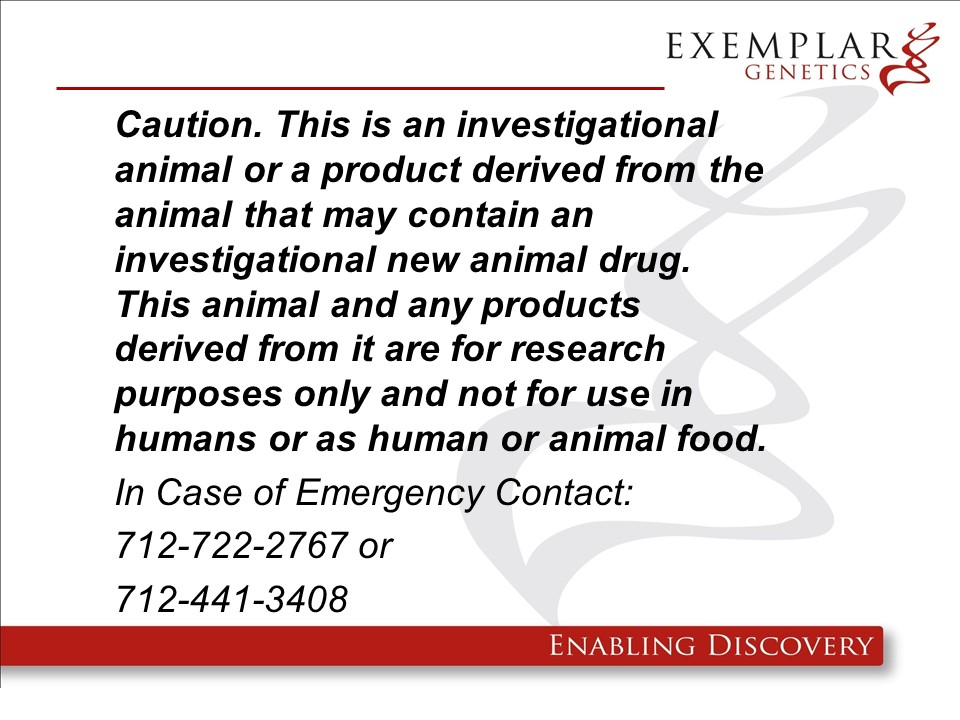 DRUG LABEL: ExeGen ATM miniswine
NDC: 86093-1801 | Form: NOT APPLICABLE
Manufacturer: Exemplar Genetics LLC (dba Precigen Exemplar)
Category: other | Type: INTENTIONAL ANIMAL GENOMIC ALTERATION LABEL
Date: 20250605

ACTIVE INGREDIENTS: HOMOZYGOUS YUCATAN MINIATURE PIG ATAXIA TELANGIECTASIA MUTATED (ATM) GENE DISRUPTED BY A ATM-NEO RDNA CONSTRUCT IN EXON 57 1 [arb'U]/1 [arb'U]

pATM-Neo in miniswine.

ExeGen ATM miniswine are geneticaly engineered yucatan miniature swine containing the rDNA construct pATM-Neo which exibit similar phenotypes to human patients with Ataxia Telangiectasia (AT). These pigs are intended to be used as large animal models of the human disease. We will not be requesting a food use authorizaiton and the carcasses and all materials generated from these animals will be destroyed by incineration.

Product Definition: A specific line of Yucatan miniature pigs (Sus scrofa domesticus), including both homozygous and heterozygous offspring resulting from a heterozygous founder in which the ATM (ataxia telangiectasia mutated) gene has been disrupted by the homologous recombinaiton of a single copy of a pATM-Neo construct in exon 57, for use in biomedical reseaarch.
Warning: This product is from a genetically engineered animal and may contain an investigational new animal drug. It is for research purposes only and not for use in humans or as food/feed unless authorization has been granted by the US Food and Drug Administration. In case of emergency or release contact Exemplar Genetics at 712-722-2767 or 712-441-3408.

See image of warning label "FDA statement 2020.jpg"